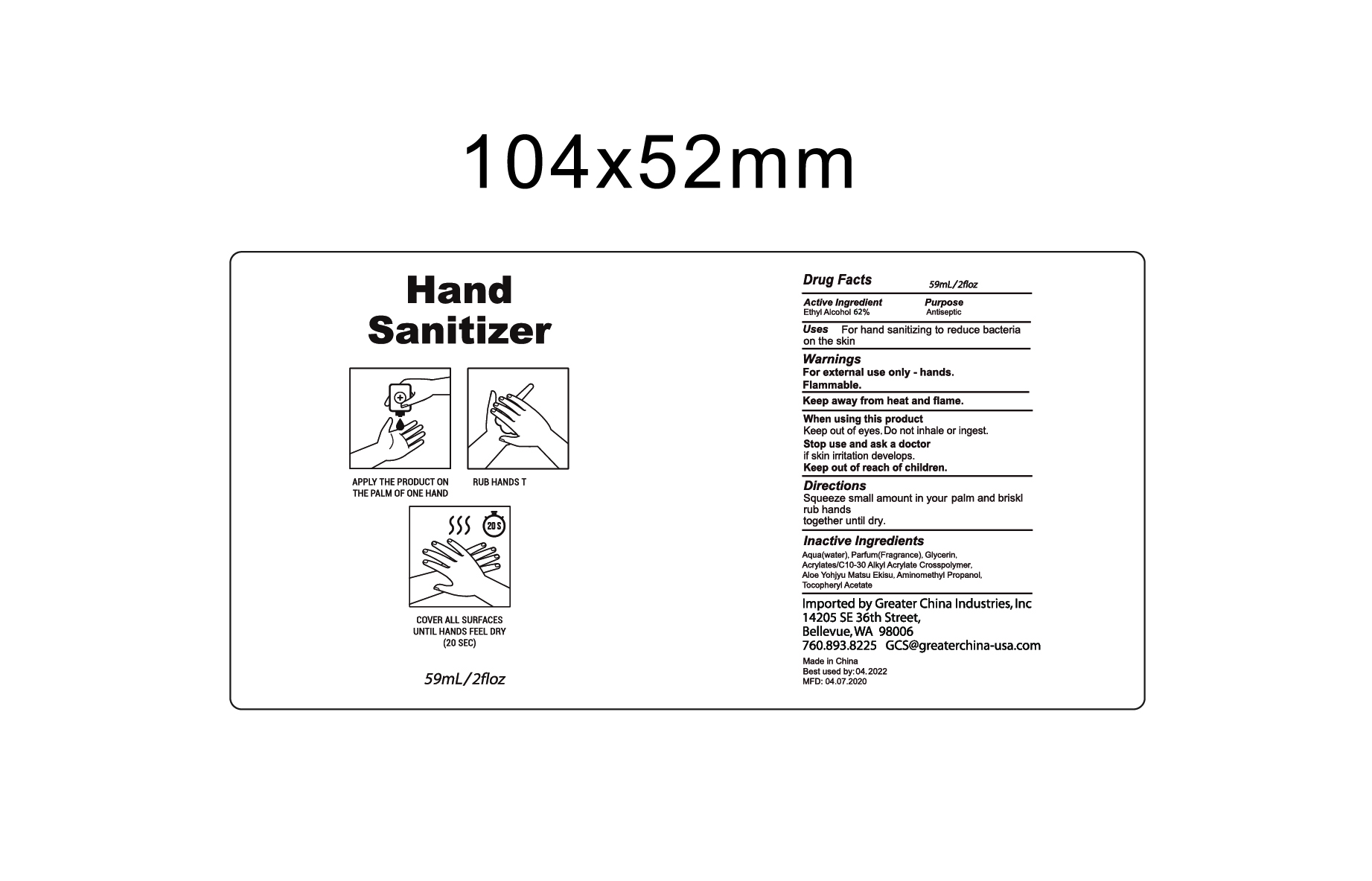 DRUG LABEL: hand sanitizer 59ml
NDC: 54860-369 | Form: GEL
Manufacturer: Shenzhen Lantern Scicence Co.,Ltd.
Category: otc | Type: HUMAN OTC DRUG LABEL
Date: 20210225

ACTIVE INGREDIENTS: ALCOHOL 62 mL/100 mL
INACTIVE INGREDIENTS: .ALPHA.-TOCOPHEROL ACETATE 0.01 mL/100 mL; ALOE ANDONGENSIS WHOLE 0.01 mL/100 mL; ALOE 0.15 mL/100 mL; CARBOMER INTERPOLYMER TYPE A (55000 CPS) 0.3 mL/100 mL; AMINOMETHYLPROPANOL 0.09 mL/100 mL; WATER 36.94 mL/100 mL; GLYCERIN 0.5 mL/100 mL

hand sanitizer 59ml

Ingredient Ingredient

Active Ingredient Purpose

Ethyl Alcohol 62%（V/V） Antiseptic

USE

For external use only-hands.

Flammable

Keep away from heat and flame.

DOSAGE AND ADMINISTRATION

Recommended for repeated use.

use anywhere without water.

Warning

For external use only-hands.

Flammable,keep away from heat and flame.

Discontinue if skin becomes irritated and ask a doctor.

Keep out of reach of children. In case of accidental ingestion,seek professional assistance or contact a Poison Control Center immediately.

WARNINGS AND PRECAUTIONS

For external use only.

Flammable, keep away from heat and flame.

STOP USE

Discontinue if skin becomes irritated and ask a doctor .

Keep out of reach of children. In case of accidental ingestion, seek professional assistance or contact a poson control center immediately.

Inactive ingredients

Aqua,Glycerin,Aloe Yohjyu Matsu Ekisu,Tocopheryl Acetate,Acrylates/C10-30 Alkyl Acrylate Crosspolymer,Aminomethyl Propanol,Parfum.

Directions

squeeze small amount in your palm and briskly rub hands together until dry.

When using this product

keep out of eyes. In case of contact with eyes, flush thoroughly with water.

Do not inhale or ingest.

Avoid contact with broken skin.

Other information

Do not store above 105F.

May discolor some fabrics.

Harmful to wood finishes and plastics.

When using this product

keep out of eyes.Do not inhale or ingest.

Stop use and ask a doctor if skin irritation develops

Keep out of reach of children.